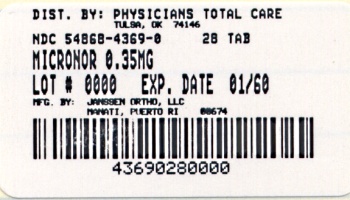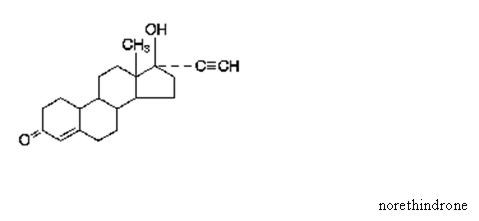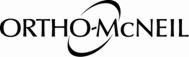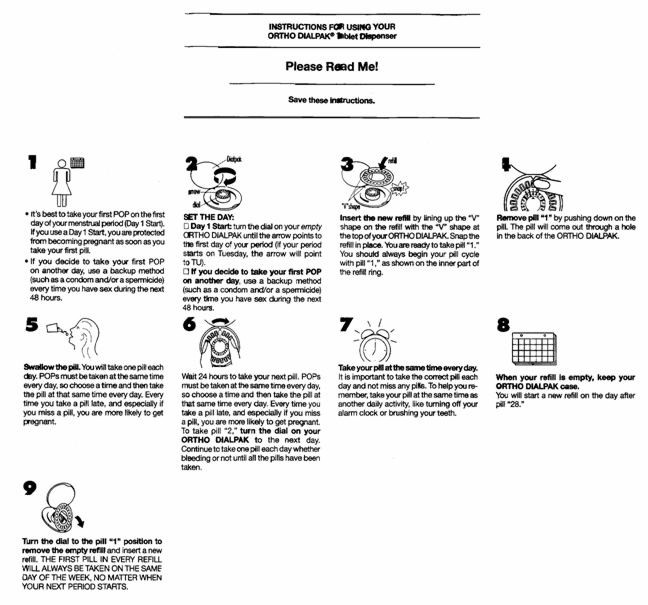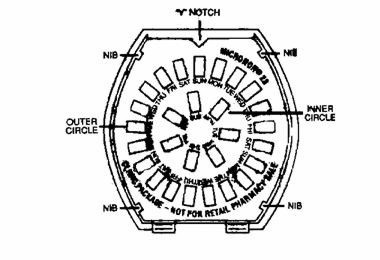 DRUG LABEL: MICRONOR
NDC: 54868-4369 | Form: TABLET
Manufacturer: Physicians Total Care, Inc.
Category: prescription | Type: HUMAN PRESCRIPTION DRUG LABEL
Date: 20110401

ACTIVE INGREDIENTS: NORETHINDRONE 0.35 mg/1 1
INACTIVE INGREDIENTS: D&C GREEN NO. 5; D&C YELLOW NO. 10; LACTOSE; MAGNESIUM STEARATE; POVIDONE; STARCH, CORN

Patients should be counseled that this product does not protect against HIV infection (AIDS) and other sexually transmitted diseases.

DESCRIPTION

Each tablet contains 0.35 mg norethindrone. Inactive ingredients include corn starch, D&C Green No. 5, D&C Yellow No. 10, lactose, magnesium stearate, and povidone.

CLINICAL PHARMACOLOGY

1. Mode of Action

ORTHO MICRONOR® progestin-only oral contraceptives prevent conception by suppressing ovulation in approximately half of users, thickening the cervical mucus to inhibit sperm penetration, lowering the midcycle LH and FSH peaks, slowing the movement of the ovum through the fallopian tubes, and altering the endometrium.

2. Pharmacokinetics

Serum progestin levels peak about two hours after oral administration, followed by rapid distribution and elimination. By 24 hours after drug ingestion, serum levels are near baseline, making efficacy dependent upon rigid adherence to the dosing schedule. There are large variations in serum levels among individual users. Progestin-only administration results in lower steady-state serum progestin levels and a shorter elimination half-life than concomitant administration with estrogens.

INDICATIONS AND USAGE

1. Indications

Progestin-only oral contraceptives are indicated for the prevention of pregnancy.

2. Efficacy

If used perfectly, the first-year failure rate for progestin-only oral contraceptives is 0.5%. However, the typical failure rate is estimated to be closer to 5%, due to late or omitted pills. Table 1 lists the pregnancy rates for users of all major methods of contraception.

Table 1: Percentage of Women Experiencing an Unintended Pregnancy During the First Year of Typical Use and the First Year of Perfect Use of Contraception and the Percentage Continuing Use at the End of the First Year. United States.
 | % of Women Experiencing an Unintended Pregnancy within the First Year of Use |  | % of Women Continuing Use at One Year*
Method (1) | Typical Use † (2) | Perfect Use‡ (3) | (4)
Chance# | 85 | 85
SpermicidesÞ | 26 | 6 | 40
Periodic abstinence | 25 |  | 63
Calendar |  | 9
Ovulation Method |  | 3
Sympto-Thermalß |  | 2
Post-Ovulation |  | 1
Capà
Parous Women | 40 | 26 | 42
Nulliparous Women | 20 | 9 | 56
Sponge
Parous Women | 40 | 20 | 42
Nulliparous Women | 20 | 9 | 56
Diaphragmà | 20 | 6 | 56
Withdrawal | 19 | 4
Condomè
Female (Reality®) | 21 | 5 | 56
Male | 14 | 3 | 61
Pill | 5 |  | 71
Progestin Only |  | 0.5
Combined |  | 0.1
IUD
Progesterone T | 2.0 | 1.5 | 81
Copper T380A | 0.8 | 0.6 | 78
LNg 20 | 0.1 | 0.1 | 81
Depo-Provera® | 0.3 | 0.3 | 70
Norplant® and Norplant-2® | 0.05 | 0.05 | 88
Female Sterilization | 0.5 | 0.5 | 100
Male Sterilization | 0.15 | 0.10 | 100

Adapted from Hatcher et al, 1998, Ref. # 1.
§ Emergency Contraceptive Pills: Treatment initiated within 72 hours after unprotected intercourse reduces the risk of pregnancy by at least 75%.
¶Lactational Amenorrhea Method: LAM is highly effective, temporary method of contraception.
Source: Trussell J, Contraceptive efficacy. In Hatcher RA, Trussell J, Stewart F, Cates W, Stewart GK, Kowal D, Guest F, Contraceptive Technology: Seventeenth Revised Edition. New York NY: Irvington Publishers, 1998.

*Among couples attempting to avoid pregnancy, the percentage who continue to use a method for one year†Among typical couples who initiate use of a method (not necessarily for the first time), the percentage who experience an accidental pregnancy during the first year if they do not stop use for any other reason. ‡Among couples who initiate use of a method (not necessarily for the first time) and who use it perfectly (both consistently and correctly), the percentage who experience an accidental pregnancy during the first year if they do not stop use for any other reason.§The treatment schedule is one dose within 72 hours after unprotected intercourse, and a second dose 12 hours after the first dose. The Food and Drug Administration has declared the following brands of oral contraceptives to be safe and effective for emergency contraception: Ovral® (1 dose is 2 white pills), Alesse® (1 dose is 5 pink pills), Nordette® or Levlen® (1 dose is 2 light-orange pills), Lo/Ovral® (1 dose is 4 white pills), Triphasil® or Tri-Levlen® (1 dose is 4 yellow pills).¶However, to maintain effective protection against pregnancy, another method of contraception must be used as soon as menstruation resumes, the frequency or duration of breastfeeds is reduced, bottle feeds are introduced, or the baby reaches six months of age.#The percents becoming pregnant in columns (2) and (3) are based on data from populations where contraception is not used and from women who cease using contraception in order to become pregnant. Among such populations, about 89% become pregnant within one year. This estimate was lowered slightly (to 85%) to represent the percent who would become pregnant within one year among women now relying on reversible methods of contraception if they abandoned contraception altogether.ÞFoams, creams, gels, vaginal suppositories, and vaginal film.ßCervical mucus (ovulation) method supplemented by calendar in the pre-ovulatory and basal body temperature in the post-ovulatory phases.àWith spermicidal cream or jelly.èWithout spermicides.
ORTHO MICRONOR® Tablets have not been studied for and are not indicated for use in emergency contraception.

CONTRAINDICATIONS

Progestin-only oral contraceptives (POPs) should not be used by women who currently have the following conditions:

- Known or suspected pregnancy
- Known or suspected carcinoma of the breast
- Undiagnosed abnormal genital bleeding
- Hypersensitivity to any component of this product
- Benign or malignant liver tumors
- Acute liver disease

WARNINGS

Cigarette smoking increases the risk of serious cardiovascular disease. Women who use oral contraceptives should be strongly advised not to smoke.

ORTHO MICRONOR® does not contain estrogen and, therefore, this insert does not discuss the serious health risks that have been associated with the estrogen component of combined oral contraceptives (COCs). The healthcare professional is referred to the prescribing information of combined oral contraceptives for a discussion of those risks. The relationship between progestin-only oral contraceptives and these risks is not fully defined. The healthcare professional should remain alert to the earliest manifestation of symptoms of any serious disease and discontinue oral contraceptive therapy when appropriate.

1. Ectopic Pregnancy

The incidence of ectopic pregnancies for progestin-only oral contraceptive users is 5 per 1000 woman-years. Up to 10% of pregnancies reported in clinical studies of progestin-only oral contraceptive users are extrauterine. Although symptoms of ectopic pregnancy should be watched for, a history of ectopic pregnancy need not be considered a contraindication to use of this contraceptive method. Healthcare professionals should be alert to the possibility of an ectopic pregnancy in women who become pregnant or complain of lower abdominal pain while on progestin-only oral contraceptives.

2. Delayed Follicular Atresia/Ovarian Cysts

If follicular development occurs, atresia of the follicle is sometimes delayed and the follicle may continue to grow beyond the size it would attain in a normal cycle. Generally these enlarged follicles disappear spontaneously. Often they are asymptomatic; in some cases they are associated with mild abdominal pain. Rarely they may twist or rupture, requiring surgical intervention.

3. Irregular Genital Bleeding

Irregular menstrual patterns are common among women using progestin-only oral contraceptives. If genital bleeding is suggestive of infection, malignancy or other abnormal conditions, such nonpharmacologic causes should be ruled out. If prolonged amenorrhea occurs, the possibility of pregnancy should be evaluated.

4. Carcinoma of the Breast and Reproductive Organs

Some epidemiological studies of oral contraceptive users have reported an increased relative risk of developing breast cancer, particularly at a younger age and apparently related to duration of use. These studies have predominantly involved combined oral contraceptives and there is insufficient data to determine whether the use of POPs similarly increases the risk.

A meta-analysis of 54 studies found a small increase in the frequency of having breast cancer diagnosed for women who were currently using combined oral contraceptives or had used them within the past ten years.

This increase in the frequency of breast cancer diagnosis, within ten years of stopping use, was generally accounted for by cancers localized to the breast. There was no increase in the frequency of having breast cancer diagnosed ten or more years after cessation of use.

Women with breast cancer should not use oral contraceptives because the role of female hormones in breast cancer has not been fully determined.

Some studies suggest that oral contraceptive use has been associated with an increase in the risk of cervical intraepithelial neoplasia in some populations of women. However, there continues to be controversy about the extent to which such findings may be due to differences in sexual behavior and other factors. There is insufficient data to determine whether the use of POPs increases the risk of developing cervical intraepithelial neoplasia.

5. Hepatic Neoplasia

Benign hepatic adenomas are associated with combined oral contraceptive use, although the incidence of benign tumors is rare in the United States. Rupture of benign, hepatic adenomas may cause death through intraabdominal hemorrhage.

Studies have shown an increased risk of developing hepatocellular carcinoma in combined oral contraceptive users. However, these cancers are rare in the U.S. There is insufficient data to determine whether POPs increase the risk of developing hepatic neoplasia.

PRECAUTIONS

1. General

Patients should be counseled that this product does not protect against HIV infection (AIDS) and other sexually transmitted diseases.

2. Physical Examination and Follow up

It is considered good medical practice for sexually active women using oral contraceptives to have annual history and physical examinations. The physical examination may be deferred until after initiation of oral contraceptives if requested by the woman and judged appropriate by the healthcare professional.

3. Carbohydrate and Lipid Metabolism

Some users may experience slight deterioration in glucose tolerance, with increases in plasma insulin but women with diabetes mellitus who use progestin-only oral contraceptives do not generally experience changes in their insulin requirements. Nonetheless, prediabetic and diabetic women in particular should be carefully monitored while taking POPs.

Lipid metabolism is occasionally affected in that HDL, HDL2, and apolipoprotein A-I and A-II may be decreased; hepatic lipase may be increased. There is usually no effect on total cholesterol, HDL3 , LDL, or VLDL.

4. Drug Interactions

The effectiveness of progestin-only pills is reduced by hepatic enzyme-inducing drugs such as the anticonvulsants phenytoin, carbamazepine, and barbiturates, and the antituberculosis drug rifampin. No significant interaction has been found with broad-spectrum antibiotics.

5. Interactions with Laboratory Tests

The following endocrine tests may be affected by progestin-only oral contraceptive use:

- Sex hormone-binding globulin (SHBG) concentrations may be decreased.
- Thyroxine concentrations may be decreased, due to a decrease in thyroid binding globulin (TBG).

6. Carcinogenesis

See WARNINGS section.

7. Pregnancy

Many studies have found no effects on fetal development associated with long-term use of contraceptive doses of oral progestins. The few studies of infant growth and development that have been conducted have not demonstrated significant adverse effects. It is nonetheless prudent to rule out suspected pregnancy before initiating any hormonal contraceptive use.

8. Nursing Mothers

In general, no adverse effects have been found on breastfeeding performance or on the health, growth or development of the infant. However, isolated post-marketing cases of decreased milk production have been reported. Small amounts of progestins pass into the breast milk of nursing mothers, resulting in detectable steroid levels in infant plasma.

9. Pediatric Use

Safety and efficacy of ORTHO MICRONOR® Tablets have been established in women of reproductive age. Safety and efficacy are expected to be the same for postpubertal adolescents under the age of 16 and for users 16 years and older. Use of this product before menarche is not indicated.

10. Fertility Following Discontinuation

The limited available data indicate a rapid return of normal ovulation and fertility following discontinuation of progestin-only oral contraceptives.

11. Headache The onset or exacerbation of migraine or development of severe headache with focal neurological symptoms which is recurrent or persistent requires discontinuation of progestin-only contraceptives and evaluation of the cause. INFORMATION FOR THE PATIENT

1. See "Detailed Patient Labeling" for detailed information.
2. Counseling issues

The following points should be discussed with prospective users before prescribing progestin-only oral contraceptives:

- The necessity of taking pills at the same time every day, includingthroughout all bleeding episodes.
- The need to use a backup method such as condoms and spermicides for the next 48 hours whenever a progestin-only oral contraceptive is taken 3 or more hours late.
- The potential side effects of progestin-only oral contraceptives, particularly menstrual irregularities.
- The need to inform the healthcare professional of prolonged episodes of bleeding, amenorrhea or severe abdominal pain.
- The importance of using a barrier method in addition to progestin-only oral contraceptives if a woman is at risk of contracting or transmitting STDs/HIV.

ADVERSE REACTIONS

Adverse reactions reported with the use of POPs include:

- Menstrual irregularity is the most frequently reported side effect.
- Frequent and irregular bleeding are common, while long duration of bleeding episodes and amenorrhea are less likely.
- Headache, breast tenderness, nausea, and dizziness are increased among progestin-only oral contraceptive users in some studies.
- Androgenic side effects such as acne, hirsutism, and weight gain occur rarely.

OVERDOSAGE

There have been no reports of serious ill effects from overdosage, including ingestion by children.

DOSAGE AND ADMINISTRATION

To achieve maximum contraceptive effectiveness, ORTHO MICRONOR® must be taken exactly as directed. One tablet is taken every day, at the same time. Administration is continuous, with no interruption between pill packs. See Detailed Patient Labeling for detailed instruction.

HOW SUPPLIED

ORTHO MICRONOR® (0.35 mg norethindrone) Tablets are available in a DIALPAK® Tablet Dispenser

(NDC 54868-4369-0) containing 28 lime green, round, flat faced, beveled edge tablets, imprinted "ORTHO 0.35" on both sides.

STORAGE: Store at 25°C (77°F); excursions permitted to 15°–30°C (59°–86°F).

Keep out of reach of children.

Relabeling of "Additional" barcode label by:
Physicians Total Care, Inc.
Tulsa, OK 74146

REFERENCES

McCann M, and Potter L. Progestin-Only Oral Contraceptives: A Comprehensive Review. Contraception, 50:60 (Suppl. 1), December 1994.

Truitt ST, Fraser A, Gallo ME, Lopez LM, Grimes DA and Schulz KF. Combined hormonal versus nonhormonal versus progestin-only contraception in lactation (Review). The Cochrane Collaboration. 2007, Issue 3.

Halderman, LD and Nelson AL. Impact of early postpartum administration of progestin-only hormonal contraceptives compared with nonhormonal contraceptives on short-term breast-feeding patterns. Am J Obstet Gynecol.; 186 (6): 1250-1258.

Ostrea EM, Mantaring III JB, Silvestre MA. Drugs that affect the fetus and newborn infant via the placenta or breast milk. Pediatr Clin N Am; 51(2004): 539-579.

Cooke ID, Back DJ, Shroff NE: Norethisterone concentration in breast milk and infant and maternal plasma during ethynodiol diactetate administration. Contraception 1985; 31:611-21.

DETAILED PATIENT LABELING

ORTHO MICRONOR® (norethindrone) Tablets

This product (like all oral contraceptives) is used to prevent pregnancy. It does not protect against HIV infection (AIDS) or other sexually transmitted diseases.

DESCRIPTION
ORTHO MICRONOR® Tablets

Each tablet contains 0.35 mg norethindrone. Inactive ingredients include corn starch, D&C Green No. 5, D&C Yellow No. 10, lactose, magnesium stearate and povidone .

INTRODUCTION

This leaflet is about birth control pills that contain one hormone, a progestin. Please read this leaflet before you begin to take your pills. It is meant to be used along with talking with your healthcare professional.

Progestin-only pills are often called "POPs" or "the minipill." POPs have less progestin than the combined birth control pill (or "the pill") which contains both an estrogen and a progestin.

HOW EFFECTIVE ARE POPs?

About 1 in 200 POP users will get pregnant in the first year if they all take POPs perfectly (that is, on time, every day). About 1 in 20 "typical" POP users (including women who are late taking pills or miss pills) gets pregnant in the first year of use. Table 2 will help you compare the efficacy of different methods.

Table 2: Percentage of Women Experiencing an Unintended Pregnancy During the First Year of Typical Use and the First Year of Perfect Use of Contraception and the Percentage Continuing Use at the End of the First Year. United States.
 | % of Women Experiencing an Unintended Pregnancy within the First Year of Use |  | % of Women Continuing Use at One Year*
Method (1) | Typical Use † (2) | Perfect Use‡ (3) | (4)
Chance# | 85 | 85
SpermicidesÞ | 26 | 6 | 40
Periodic abstinence | 25 |  | 63
Calendar |  | 9
Ovulation Method |  | 3
Sympto-Thermalß |  | 2
Post-Ovulation |  | 1
Capà
Parous Women | 40 | 26 | 42
Nulliparous Women | 20 | 9 | 56
Sponge
Parous Women | 40 | 20 | 42
Nulliparous Women | 20 | 9 | 56
Diaphragmà | 20 | 6 | 56
Withdrawal | 19 | 4
Condomè
Female (Reality®) | 21 | 5 | 56
Male | 14 | 3 | 61
Pill | 5 |  | 71
Progestin Only |  | 0.5
Combined |  | 0.1
IUD
Progesterone T | 2.0 | 1.5 | 81
Copper T380A | 0.8 | 0.6 | 78
LNg 20 | 0.1 | 0.1 | 81
Depo-Provera® | 0.3 | 0.3 | 70
Norplant® and Norplant-2® | 0.05 | 0.05 | 88
Female Sterilization | 0.5 | 0.5 | 100
Male Sterilization | 0.15 | 0.10 | 100

Adapted from Hatcher et al, 1998, Ref. # 1.

Emergency Contraceptive Pills: Treatment initiated within 72 hours after unprotected intercourse reduces the risk of pregnancy by at least 75%.§Lactational Amenorrhea Method: LAM is highly effective, temporary method of contraception.¶

Source: Trussell J, Contraceptive efficacy. In Hatcher RA, Trussell J, Stewart F, Cates W, Stewart GK, Kowal D, Guest F, Contraceptive Technology: Seventeenth Revised Edition. New York NY: Irvington Publishers, 1998.

*Among couples attempting to avoid pregnancy, the percentage who continue to use a method for one year.†Among typical couples who initiate use of a method (not necessarily for the first time), the percentage who experience an accidental pregnancy during the first year if they do not stop use for any other reason.‡Among couples who initiate use of a method (not necessarily for the first time) and who use it perfectly (both consistently and correctly), the percentage who experience an accidental pregnancy during the first year if they do not stop use for any other reason.§The treatment schedule is one dose within 72 hours after unprotected intercourse, and a second dose 12 hours after the first dose. The Food and Drug Administration has declared the following brands of oral contraceptives to be safe and effective for emergency contraception: Ovral® (1 dose is 2 white pills), Alesse® (1 dose is 5 pink pills), Nordette® or Levlen® (1 dose is 2 light-orange pills), Lo/Ovral® (1 dose is 4 white pills), Triphasil® or Tri-Levlen® (1 dose is 4 yellow pills).¶However, to maintain effective protection against pregnancy, another method of contraception must be used as soon as menstruation resumes, the frequency or duration of breastfeeds is reduced, bottle feeds are introduced, or the baby reaches six months of age.#The percents becoming pregnant in columns (2) and (3) are based on data from populations where contraception is not used and from women who cease using contraception in order to become pregnant. Among such populations, about 89% become pregnant within one year. This estimate was lowered slightly (to 85%) to represent the percent who would become pregnant within one year among women now relying on reversible methods of contraception if they abandoned contraception altogether.ÞFoams, creams, gels, vaginal suppositories, and vaginal film.ßCervical mucus (ovulation) method supplemented by calendar in the pre-ovulatory and basal body temperature in the post-ovulatory phases.àWith spermicidal cream or jelly.èWithout spermicides.

ORTHO MICRONOR® Tablets have not been studied for and are not indicated for use in emergency contraception.

HOW DO POPs WORK?

POPs can prevent pregnancy in different ways including:

- They make the cervical mucus at the entrance to the womb (the uterus) too thick for the sperm to get through to the egg.
- They prevent ovulation (release of the egg from the ovary) in about half of the cycles.
- They also affect other hormones, the fallopian tubes and the lining of the uterus.

YOU SHOULD NOT TAKE POPs

- If there is any chance you may be pregnant.
- If you have breast cancer.
- If you have bleeding between your periods that has not been diagnosed.
- If you are taking certain drugs for epilepsy (seizures) or for TB. (See "Using POPs with Other Medicines" below.)
- If you are hypersensitive, or allergic, to any component of this product.
- If you have liver tumors, either benign or cancerous.
- If you have acute liver disease.

RISKS OF TAKING POPs

Cigarette smoking greatly increases the possibility of suffering heart attacks and strokes. Women who use oral contraceptives are strongly advised not to smoke.

WARNING:

If you have sudden or severe pain in your lower abdomen or stomach area, you may have an ectopic pregnancy or an ovarian cyst. If this happens, you should contact your healthcare professional immediately.

Ectopic Pregnancy

An ectopic pregnancy is a pregnancy outside the womb. Because POPs protect against pregnancy, the chance of having a pregnancy outside the womb is very low. If you do get pregnant while taking POPs, you have a slightly higher chance that the pregnancy will be ectopic than do users of some other birth control methods.

Ovarian Cysts

These cysts are small sacs of fluid in the ovary. They are more common among POP users than among users of most other birth control methods. They usually disappear without treatment and rarely cause problems.

Cancer of the Reproductive Organs and Breasts

Some studies in women who use combined oral contraceptives that contain both estrogen and a progestin have reported an increase in the risk of developing breast cancer, particularly at a younger age and apparently related to duration of use. There is insufficient data to determine whether the use of POPs similarly increases this risk.

A meta-analysis of 54 studies found a small increase in the frequency of having breast cancer diagnosed for women who were currently using combined oral contraceptives or had used them within the past ten years. This increase in the frequency of breast cancer diagnosis, within ten years of stopping use, was generally accounted for by cancers localized to the breast. There was no increase in the frequency of having breast cancer diagnosed ten or more years after cessation of use.

Some studies have found an increase in the incidence of cancer of the cervix in women who use oral contraceptives. However, this finding may be related to factors other than the use of oral contraceptives and there is insufficient data to determine whether the use of POPs increases the risk of developing cancer of the cervix.

Liver Tumors

In rare cases, combined oral contraceptives can cause benign but dangerous liver tumors. These benign liver tumors can rupture and cause fatal internal bleeding. In addition, some studies report an increased risk of developing liver cancer among women who use combined oral contraceptives. However, liver cancers are rare. There is insufficient data to determine whether POPs increase the risk of liver tumors.

Diabetic Women

Diabetic women taking POPs do not generally require changes in the amount of insulin they are taking. However, your healthcare professional may monitor you more closely under these conditions.

SEXUALLY TRANSMITTED DISEASES (STDs)

WARNING: POPs do not protect against getting or giving someone HIV (AIDS) or any other STD, such as chlamydia, gonorrhea, genital warts or herpes.

SIDE EFFECTS

Irregular Bleeding:

The most common side effect of POPs is a change in menstrual bleeding. Your periods may be either early or late, and you may have some spotting between periods. Taking pills late or missing pills can result in some spotting or bleeding.

Other Side Effects:

Less common side effects include headaches, tender breasts, nausea and dizziness. Weight gain, acne and extra hair on your face and body have been reported, but are rare.

If you are concerned about any of these side effects, check with your healthcare professional.

USING POPs WITH OTHER MEDICINES

Before taking a POP, inform your healthcare professional of any other medication, including over-the-counter medicine, that you may be taking.

These medicines can make POPs less effective:

Medicines for seizures such as:

- Phenytoin (Dilantin®)
- Carbamazepine (Tegretol)
- Phenobarbital

Medicine for TB:

- Rifampin (Rifampicin)

Before you begin taking any new medicines be sure your healthcare professional knows you are taking a progestin-only birth control pill.

HOW TO TAKE POPs

IMPORTANT POINTS TO REMEMBER

- POPs must be taken at the same time every day, so choose a time and then take the pill at that same time every day. Every time you take a pill late, and especially if you miss a pill, you are more likely to get pregnant.
- Start the next pack the day after the last pack is finished. There is no break between packs. Always have your next pack of pills ready.
- You may have some menstrual spotting between periods. Do not stop taking your pills if this happens.
- If you vomit soon after taking a pill, use a backup method (such as a condom and/or a spermicide) for 48 hours.
- If you want to stop taking POPs, you can do so at any time, but, if you remain sexually active and don't wish to become pregnant, be certain to use another birth control method.
- If you are not sure about how to take POPs, ask your healthcare professional.

STARTING POPs

- It's best to take your first POP on the first day of your menstrual period.
- If you decide to take your first POP on another day, use a backup method (such as a condom and/or a spermicide) every time you have sex during the next 48 hours.
- If you have had a miscarriage or an abortion, you can start POPs the next day.

IF YOU ARE LATE OR MISS TAKING YOUR POPs

- If you are more than 3 hours late or you miss one or more POPs: 1)TAKE a missed pill as soon as you remember that you missed it,2)THEN go back to taking POPs at your regular time,3)BUT be sure to use a backup method (such as a condom and/or a spermicide) every time you have sex for the next 48 hours.
- If you are not sure what to do about the pills you have missed, keep taking POPs and use a backup method until you can talk to your healthcare professional.

IF YOU ARE BREASTFEEDING

- If you are fully breastfeeding (not giving your baby any food or formula), you may start your pills 6 weeks after delivery.
- If you are partially breastfeeding (giving your baby some food or formula), you should start taking pills by 3 weeks after delivery.

IF YOU ARE SWITCHING PILLS

- If you are switching from the combined pills to POPs, take the first POP the day after you finish the last active combined pill. Do not take any of the 7 inactive pills from the combined pill pack. You should know that many women have irregular periods after switching to POPs, but this is normal and to be expected.
- If you are switching from POPs to the combined pills, take the first active combined pill on the first day of your period, even if your POPs pack is not finished.
- If you switch to another brand of POPs, start the new brand anytime.
- If you are breastfeeding, you can switch to another method of birth control at any time, except do not switch to the combined pills until you stop breastfeeding or at least until 6 months after delivery.

PREGNANCY WHILE ON THE PILL

If you think you are pregnant, contact your healthcare professional. Even though research has shown that POPs do not cause harm to the unborn baby, it is always best not to take any drugs or medicines that you don't need when you are pregnant.

You should get a pregnancy test:

- If your period is late and you took one or more pills late or missed taking them and had sex without a backup method.
- Anytime it has been more than 45 days since the beginning of your last period.

WILL POPs AFFECT YOUR ABILITY TO GET PREGNANT LATER?

If you want to become pregnant, simply stop taking POPs. POPs will not delay your ability to get pregnant.

BREASTFEEDING

If you are breastfeeding, POPs will not affect the quality or amount of your breastmilk or the health of your nursing baby. However, isolated cases of decreased milk production have been reported.

OVERDOSE

No serious problems have been reported when many pills were taken by accident, even by a small child, so there is usually no reason to treat an overdose.

OTHER QUESTIONS OR CONCERNS

If you have any questions or concerns, check with yourhealthcare professional. You can also ask for the more detailed "Professional Labeling" written for doctors and other healthcare professionals.

HOW TO STORE YOUR POPs

Store at 25°C (77°F); excursions permitted to 15°–30°C (59°–86°F).

Rx only

Keep out of reach of children.

ORTHO-McNEIL
PHARMACEUTICAL, INC.

Raritan, New Jersey 08869

©OMP 1998

PRINTED IN U.S.A.
ISSUED June, 2008
635-50-894

If you are late or you miss taking your POPs:

- If you are more than 3 hours late or you miss one or more POPs: 1)TAKE a missed pill as soon as you remember that you missed it,2)THEN go back to taking POPs at your regular time,3)BUT be sure to use a backup method (such as a condom and/or a spermicide) every time you have sex for the next 48 hours.
- If you are not sure what to do about the pills you have missed, keep taking POPs and use a backup method until you can talk to your healthcare professional.

Important points to remember:

- POPs must be taken at the same time every day, so choose a time and then take the pill at that same time every day. Every time you take a pill late, and especially if you miss a pill, you are more likely to get pregnant.
- Start the next pack the day after the last pack is finished. There is no break between packs. Always have your next pack of pills ready.
- You may have some menstrual spotting between periods. Do not stop taking your pills if this happens.
- If you vomit soon after taking a pill, use a backup method (such as a condom and/or a spermicide) for 48 hours.
- If you want to stop taking POPs, you can do so at any time, but, if you remain sexually active and don't wish to become pregnant, be certain to use another birth control method.
- If you are not sure about how to take POPs, ask your healthcare professional.

INSTRUCTIONS FOR USE
VERIDATE® Tablet Dispenser-28's

1. Place the refill in the VERIDATE so that the V notch in the refill is at the top of the dispenser (see drawing). Press the refill down so that it fits firmly under all nibs.

2. The first time you use these pills, take your first pill on the first day of your menstrual period.

3. Choose a pill that corresponds with the day of the week on which you are taking the first pill.

4. Continue taking one pill daily, clockwise, until no pills remain in the outer circle. It is important that you take your pills at the same time every day.

5. The next day, take a pill from the inner circle that corresponds with the day of the week it happens to be. Take a pill each day until all seven are taken.

6. After you have taken all 28 pills, insert a new refill in the veridate and begin taking your pills again the next day. Be sure the calendar day on the package corresponds with the actual day.

ORTHO-MCNEIL PHARMACEUTICAL, INC.

Raritan, New Jersey 08869

©OMP 2001

PRINTED IN U.S.A.
Issued June 2008
651-50-895-X

PRINCIPAL DISPLAY PANEL

MICRONOR® (0.35 mg norethindrone) Tablets

NDC 54868-4369-0